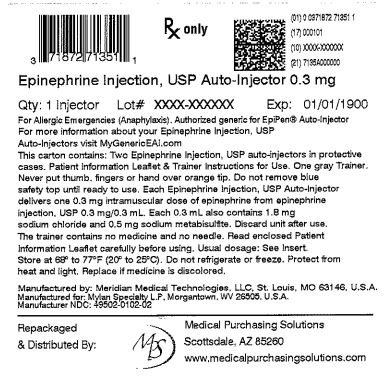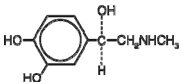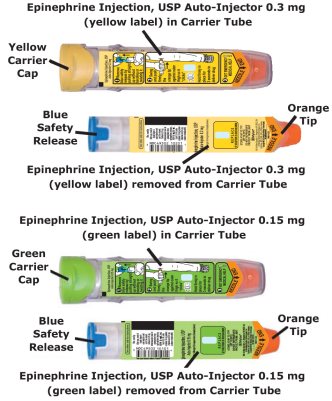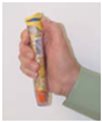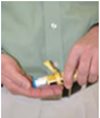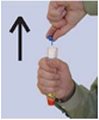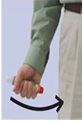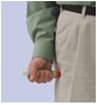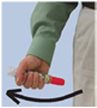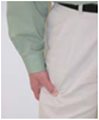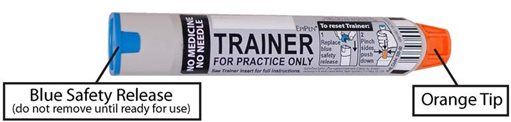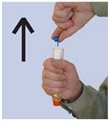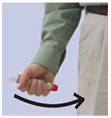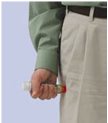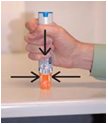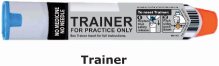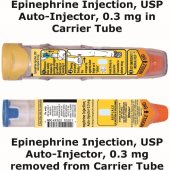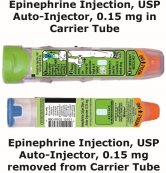 DRUG LABEL: Epinephrine
NDC: 71872-7135 | Form: INJECTION
Manufacturer: Medical Purchasing Solutions, LLC
Category: prescription | Type: HUMAN PRESCRIPTION DRUG LABEL
Date: 20230522

ACTIVE INGREDIENTS: EPINEPHRINE 0.3 mg/0.3 mL
INACTIVE INGREDIENTS: SODIUM CHLORIDE; SODIUM METABISULFITE; HYDROCHLORIC ACID; WATER

HIGHLIGHTS OF PRESCRIBING INFORMATION

These highlights do not include all the information needed to use EPINEPHRINE INJECTION, USP AUTO- INJECTOR safely and effectively. See full prescribing information for EPINEPHRINE INJECTION, USP AUTO- INJECTOR.
EPINEPHRINE injection, USP Auto-Injector, 0.15 mg, 0.3 mg, for intramuscular or subcutaneous use
Initial U.S. Approval: 1939

RECENT MAJOR CHANGES

- Dosage and Administration (2) 05/2016
- Warnings and Precautions (5.2, 5.3) 05/2016

1 INDICATIONS AND USAGE

Epinephrine injection, USP auto-injector contains epinephrine, a non-selective alpha and beta-adrenergic receptor agonist, indicated in the emergency treatment of allergic reactions (Type I) including anaphylaxis. (1)

2 DOSAGE AND ADMINISTRATION

- Patients greater than or equal to 30 kg (66 lbs): epinephrine injection, USP auto-injector, 0.3 mg (2)
- Patients 15 to 30 kg (33 lbs to 66 lbs): epinephrine injection, USP auto-injector, 0.15 mg (2)

Inject intramuscularly or subcutaneously into the anterolateral aspect of the thigh, through clothing if necessary. Each device is a single-use injection . (2)

3 DOSAGE FORMS AND STRENGTHS

- Epinephrine injection, USP auto-injector: 0.3 mg: 0.3 mg/0.3 mL epinephrine, USP, pre-filled auto-injector (3)
- Epinephrine injection, USP auto-injector: 0.15 mg: 0.15 mg/0.3 mL epinephrine, USP, pre-filled auto-injector (3)

4 CONTRAINDICATIONS

None (4)

5 WARNINGS AND PRECAUTIONS

- In conjunction with use, seek immediate medical or hospital care. (5.1)
- Do not inject intravenously, into buttock, or into digits, hands, or feet. (5.2)
- To minimize the risk of injection related injury, instruct caregivers to hold the child’s leg firmly in place and limit movement prior to and during injection when administering to young children. (5.2)
- Rare cases of serious skin and soft tissue infections have been reported following epinephrine injection. Advise patients to seek medical care if they develop signs or symptoms of infection. (5.3)
- The presence of a sulfite in this product should not deter use. (5.4)
- Administer with caution in patients with heart disease; may aggravate angina pectoris or produce ventricular arrhythmias. (5.5)

6 ADVERSE REACTIONS

Adverse reactions to epinephrine include anxiety, apprehensiveness, restlessness, tremor, weakness, dizziness, sweating, palpitations, pallor, nausea and vomiting, headache, and/or respiratory difficulties. (6)

To report SUSPECTED ADVERSE REACTIONS, contact Mylan Specialty, L.P. at 1-877-446-3679 (1-877-4-INFO-RX) or FDA at 1-800-FDA-1088 or www.fda.gov/medwatch.

7 DRUG INTERACTIONS

- Cardiac glycosides or diuretics: observe for development of cardiac arrhythmias. (7)
- Tricyclic antidepressants, monoamine oxidase inhibitors, levothyroxine sodium, and certain antihistamines: potentiate effects of epinephrine. (7)
- Beta-adrenergic blocking drugs: antagonize cardiostimulating and bronchodilating effects of epinephrine. (7)
- Alpha-adrenergic blocking drugs: antagonize vasoconstricting and hypertensive effects of epinephrine. (7)
- Ergot alkaloids: may reverse the pressor effects of epinephrine. (7)

8 USE IN SPECIFIC POPULATIONS

- Elderly patients may be at greater risk of developing adverse reactions. (5.5, 8.5)

FULL PRESCRIBING INFORMATION

1 INDICATIONS AND USAGE

Epinephrine injection, USP auto-injectors are indicated in the emergency treatment of allergic reactions (Type I) including anaphylaxis to stinging insects (e.g., order Hymenoptera, which include bees, wasps, hornets, yellow jackets and fire ants) and biting insects (e.g., triatoma, mosquitoes), allergen immunotherapy, foods, drugs, diagnostic testing substances (e.g., radiocontrast media) and other allergens, as well as idiopathic anaphylaxis or exercise-induced anaphylaxis.

Epinephrine injection, USP auto-injectors are intended for immediate administration in patients who are determined to be at increased risk for anaphylaxis, including individuals with a history of anaphylactic reactions.

Anaphylactic reactions may occur within minutes after exposure and consist of flushing, apprehension, syncope, tachycardia, thready or unobtainable pulse associated with a fall in blood pressure, convulsions, vomiting, diarrhea and abdominal cramps, involuntary voiding, wheezing, dyspnea due to laryngeal spasm, pruritus, rashes, urticaria or angioedema.

Epinephrine injection, USP auto-injectors are intended for immediate administration as emergency supportive therapy only and are not a substitute for immediate medical care.

2 DOSAGE AND ADMINISTRATION

Selection of the appropriate epinephrine injection, USP auto-injector is determined according to patient body weight.

- Patients greater than or equal to 30 kg (approximately 66 pounds or more): epinephrine injection, USP auto-injector, 0.3 mg
- Patients 15 kg to 30 kg (33 pounds to 66 pounds): epinephrine injection, USP auto-injector, 0.15 mg

Inject epinephrine injection, USP auto-injector intramuscularly or subcutaneously into the anterolateral aspect of the thigh, through clothing if necessary. Instruct caregivers of young children who are prescribed an epinephrine injection, USP auto-injector and who may be uncooperative and kick or move during an injection to hold the leg firmly in place and limit movement prior to and during an injection [ see Warnings and Precautions (5.2)].

Each epinephrine injection, USP auto-injector contains a single dose of epinephrine for single-use injection. Since the doses of epinephrine delivered from epinephrine injection, USP auto-injector are fixed, consider using other forms of injectable epinephrine if doses lower than 0.15 mg are deemed necessary.

The prescriber should carefully assess each patient to determine the most appropriate dose of epinephrine, recognizing the life-threatening nature of the reactions for which this drug is indicated. With severe persistent anaphylaxis, repeat injections with an additional epinephrine injection, USP auto-injector may be necessary. More than two sequential doses of epinephrine should only be administered under direct medical supervision [ see Warnings and Precautions (5.1)].

The epinephrine solution in the clear window of the epinephrine injection, USP auto-injector should be inspected visually for particulate matter and discoloration. Epinephrine is light sensitive and should be stored in the carrier tube provided to protect it from light [ see How Supplied/Storage and Handling (16.2)] .

3 DOSAGE FORMS AND STRENGTHS

- Injection, 0.3 mg/0.3 mL epinephrine injection, USP, pre-filled auto-injector
- Injection, 0.15 mg/0.3 mL epinephrine injection, USP, pre-filled auto-injector

4 CONTRAINDICATIONS

None

5 WARNINGS AND PRECAUTIONS

5.1 Emergency Treatment

Epinephrine injection, USP auto-injectors are intended for immediate administration as emergency supportive therapy and are not intended as a substitute for immediate medical care. In conjunction with the administration of epinephrine, the patient should seek immediate medical or hospital care. More than two sequential doses of epinephrine should only be administered under direct medical supervision [ see Indications and Usage (1), Dosage and Administration (2) and Patient Counseling Information (17)].

5.2 Injection-Related Complications

Epinephrine injection, USP auto-injector should only be injected into the anterolateral aspect of the thigh [ see Dosage and Administration (2) and Patient Counseling Information (17)].

- Do not inject intravenously. Large doses or accidental intravenous injection of epinephrine may result in cerebral hemorrhage due to sharp rise in blood pressure. Rapidly acting vasodilators can counteract the marked pressor effects of epinephrine if there is such inadvertent administration.
- Do not inject into buttock. Injection into the buttock may not provide effective treatment of anaphylaxis. Advise the patient to go immediately to the nearest emergency room for further treatment of anaphylaxis. Additionally, injection into the buttock has been associated with Clostridial infections (gas gangrene). Cleansing with alcohol does not kill bacterial spores, and therefore, does not lower this risk.
- Do not inject into digits, hands or feet. Since epinephrine is a strong vasoconstrictor, accidental injection into the digits, hands or feet may result in loss of blood flow to the affected area. Advise the patient to go immediately to the nearest emergency room and to inform the healthcare provider in the emergency room of the location of the accidental injection. Treatment of such inadvertent administration should consist of vasodilation, in addition to further appropriate treatment of anaphylaxis [ see Adverse Reactions (6)].
- Hold leg firmly during injection. Lacerations, bent needles, and embedded needles have been reported when epinephrine injection, USP auto-injector has been injected into the thigh of young children who are uncooperative and kick or move during an injection. To minimize the risk of injection related injury when administering epinephrine injection, USP auto-injector to young children, instruct caregivers to hold the child’s leg firmly in place and limit movement prior to and during injection.

5.3 Serious Infections at the Injection Site

Rare cases of serious skin and soft tissue infections, including necrotizing fasciitis and myonecrosis caused by Clostridia (gas gangrene), have been reported at the injection site following epinephrine injection for anaphylaxis. Clostridium spores can be present on the skin and introduced into the deep tissue with subcutaneous or intramuscular injection. While cleansing with alcohol may reduce presence of bacteria on the skin, alcohol cleansing does not kill Clostridium spores. To decrease the risk of Clostridium infection, do not inject epinephrine injection, USP auto-injector into the buttock [see Warnings and Precautions (5.2)]. Advise patients to seek medical care if they develop signs or symptoms of infection, such as persistent redness, warmth, swelling, or tenderness, at the epinephrine injection site.

5.4 Allergic Reactions Associated with Sulfite

The presence of a sulfite in this product should not deter administration of the drug for treatment of serious allergic or other emergency situations even if the patient is sulfite-sensitive.

Epinephrine is the preferred treatment for serious allergic reactions or other emergency situations even though this product contains sodium metabisulfite, a sulfite that may, in other products, cause allergic-type reactions including anaphylactic symptoms or life-threatening or less severe asthmatic episodes in certain susceptible persons.

The alternatives to using epinephrine in a life-threatening situation may not be satisfactory.

5.5 Disease Interactions

Some patients may be at greater risk for developing adverse reactions after epinephrine administration. Despite these concerns, it should be recognized that the presence of these conditions is not a contraindication to epinephrine administration in an acute, life-threatening situation. Therefore, patients with these conditions, and/or any other person who might be in a position to administer epinephrine injection, USP auto-injector to a patient experiencing anaphylaxis should be carefully instructed in regard to the circumstances under which epinephrine should be used.

- Patients with Heart Disease

Epinephrine should be administered with caution to patients who have heart disease, including patients with cardiac arrhythmias, coronary artery or organic heart disease, or hypertension . In such patients, or in patients who are on drugs that may sensitize the heart to arrhythmias , epinephrine may precipitate or aggravate angina pectoris as well as produce ventricular arrhythmias [ see Drug Interactions (7) and Adverse Reactions (6)].

- Other Patients and Diseases

Epinephrine should be administered with caution to patients with hyperthyroidism, diabetes, elderly individuals, and pregnant women. Patients with Parkinson’s disease may notice a temporary worsening of symptoms.

6 ADVERSE REACTIONS

Due to the lack of randomized, controlled clinical trials of epinephrine for the treatment of anaphylaxis, the true incidence of adverse reactions associated with the systemic use of epinephrine is difficult to determine. Adverse reactions reported in observational trials, case reports, and studies are listed below.

Common adverse reactions to systemically administered epinephrine include anxiety; apprehensiveness; restlessness; tremor; weakness; dizziness; sweating; palpitations; pallor; nausea and vomiting; headache; and/or respiratory difficulties. These symptoms occur in some persons receiving therapeutic doses of epinephrine, but are more likely to occur in patients with hypertension or hyperthyroidism [ see Warnings and Precautions (5.5)].

Arrhythmias, including fatal ventricular fibrillation, have been reported, particularly in patients with underlying cardiac disease or those receiving certain drugs [ see Warnings and Precautions (5.5) and Drug Interactions (7)].

Rapid rises in blood pressure have produced cerebral hemorrhage, particularly in elderly patients with cardiovascular disease [ see Warnings and Precautions (5.5)].

Angina may occur in patients with coronary artery disease [ see Warnings and Precautions (5.5)].

Rare cases of stress cardiomyopathy have been reported in patients treated with epinephrine.

Accidental injection into the digits, hands or feet may result in loss of blood flow to the affected area [ see Warnings and Precautions (5.2)].

Adverse events experienced as a result of accidental injections may include increased heart rate, local reactions including injection site pallor, coldness and hypoesthesia or injury at the injection site resulting in bruising, bleeding, discoloration, erythema or skeletal injury.

Lacerations, bent needles, and embedded needles have been reported when epinephrine injection, USP auto-injector has been injected into the thigh of young children who are uncooperative and kick or move during the injection [ see Warning and Precautions (5.2)].

Injection into the buttock has resulted in cases of gas gangrene [ see Warnings and Precautions (5.2)] .

Rare cases of serious skin and soft tissue infections, including necrotizing fasciitis and myonecrosis caused by Clostridia (gas gangrene), have been reported following epinephrine injection, including epinephrine injection, USP auto-injector, in the thigh [ see Warnings and Precautions (5.3)].

7 DRUG INTERACTIONS

Patients who receive epinephrine while concomitantly taking cardiac glycosides, diuretics, or anti-arrhythmics should be observed carefully for the development of cardiac arrhythmias [ see Warnings and Precautions (5.5)].

The effects of epinephrine may be potentiated by tricyclic antidepressants, monoamine oxidase inhibitors, levothyroxine sodium, and certain antihistamines, notably chlorpheniramine, tripelennamine, and diphenhydramine.

The cardiostimulating and bronchodilating effects of epinephrine are antagonized by beta- adrenergic blocking drugs, such as propranolol.

The vasoconstricting and hypertensive effects of epinephrine are antagonized by alpha- adrenergic blocking drugs, such as phentolamine.

Ergot alkaloids may also reverse the pressor effects of epinephrine.

8 USE IN SPECIFIC POPULATIONS

8.1 Pregnancy

Teratogenic Effects

Pregnancy Category C

There are no adequate and well controlled studies of the acute effect of epinephrine in pregnant women.

Epinephrine was teratogenic in rabbits, mice and hamsters. Epinephrine should be used during pregnancy only if the potential benefit justifies the potential risk to the fetus (fetal anoxia, spontaneous abortion, or both).

Epinephrine has been shown to have teratogenic effects when administered subcutaneously in rabbits at approximately 30 times the maximum recommended daily subcutaneous or intramuscular dose (on a mg/m^2 basis at a maternal dose of 1.2 mg/kg/day for two to three days), in mice at approximately 7 times the maximum daily subcutaneous or intramuscular dose (on a mg/m^2 basis at a maternal subcutaneous dose of 1 mg/kg/day for 10 days), and in hamsters at approximately 5 times the maximum recommended daily subcutaneous or intramuscular dose (on a mg/m^2 basis at a maternal subcutaneous dose of 0.5 mg/kg/day for 4 days).

These effects were not seen in mice at approximately 3 times the maximum recommended daily subcutaneous or intramuscular dose (on a mg/m^2 basis at a subcutaneous maternal dose of 0.5 mg/kg/day for 10 days).

8.3 Nursing Mothers

It is not known whether epinephrine is excreted in human milk. Because many drugs are excreted in human milk, caution should be exercised when epinephrine injection, USP auto-injector is administered to a nursing woman.

8.4 Pediatric Use

Epinephrine injection, USP auto-injector may be administered to pediatric patients at a dosage appropriate to body weight [ see Dosage and Administration (2)] . Clinical experience with the use of epinephrine suggests that the adverse reactions seen in children are similar in nature and extent to those both expected and reported in adults. Since the doses of epinephrine delivered from epinephrine injection, USP auto-injectors are fixed, consider using other forms of injectable epinephrine if doses lower than 0.15 mg are deemed necessary.

8.5 Geriatric Use

Clinical studies for the treatment of anaphylaxis have not been performed in subjects aged 65 and over to determine whether they respond differently from younger subjects. However, other reported clinical experience with use of epinephrine for the treatment of anaphylaxis has identified that geriatric patients may be particularly sensitive to the effects of epinephrine. Therefore, epinephrine injection, USP auto-injector should be administered with caution in elderly individuals, who may be at greater risk for developing adverse reactions after epinephrine administration [ see Warnings and Precautions (5.5), Overdosage (10)].

10 OVERDOSAGE

Overdosage of epinephrine may produce extremely elevated arterial pressure, which may result in cerebrovascular hemorrhage, particularly in elderly patients. Overdosage may also result in pulmonary edema because of peripheral vascular constriction together with cardiac stimulation. Treatment consists of rapidly acting vasodilators or alpha-adrenergic blocking drugs and/or respiratory support.

Epinephrine overdosage can also cause transient bradycardia followed by tachycardia, and these may be accompanied by potentially fatal cardiac arrhythmias. Premature ventricular contractions may appear within one minute after injection and may be followed by multifocal ventricular tachycardia (prefibrillation rhythm). Subsidence of the ventricular effects may be followed by atrial tachycardia and occasionally by atrioventricular block. Treatment of arrhythmias consists of administration of a beta-adrenergic blocking drug such as propranolol.

Overdosage sometimes results in extreme pallor and coldness of the skin, metabolic acidosis, and kidney failure. Suitable corrective measures must be taken in such situations.

11 DESCRIPTION

Epinephrine injection, USP auto-injectors, 0.3 mg and 0.15 mg, are auto-injectors and combination products containing drug and device components.

Each epinephrine injection, USP auto-injector, 0.3 mg delivers a single dose of 0.3 mg epinephrine from epinephrine injection, USP 0.3 mg/0.3 mL in a sterile solution.

Each epinephrine injection, USP auto-injector, 0.15 mg delivers a single dose of 0.15 mg epinephrine from epinephrine injection, USP 0.15 mg/0.3 mL in a sterile solution.

The epinephrine injection, USP auto-injector contains 2 mL epinephrine solution. Approximately 1.7 mL remains in the auto-injector after activation, but is not available for future use, and should be discarded.

Each 0.3 mL in the epinephrine injection, USP auto-injector, 0.3 mg contains 0.3 mg epinephrine, 1.8 mg sodium chloride, 0.5 mg sodium metabisulfite, hydrochloric acid to adjust pH, and Water for Injection. The pH range is 2.2-5.0.

Each 0.3 mL in the epinephrine injection, USP auto-injector, 0.15 mg contains 0.15 mg epinephrine, 1.8 mg sodium chloride, 0.5 mg sodium metabisulfite, hydrochloric acid to adjust pH, and Water for Injection. The pH range is 2.2-5.0.

Epinephrine is a sympathomimetic catecholamine. Chemically, epinephrine is (-)-3,4- Dihydroxy-α-[(methylamino)methyl]benzyl alcohol with the following structure:

Epinephrine solution deteriorates rapidly on exposure to air or light, turning pink from oxidation to adrenochrome and brown from the formation of melanin. Replace epinephrine injection, USP auto-injector if the epinephrine solution appears discolored (pinkish or brown color), cloudy, or contains particles.

Thoroughly review the patient instructions and operation of epinephrine injection, USP auto-injector with patients and caregivers prior to use [ see Patient Counseling Information (17)].

12 CLINICAL PHARMACOLOGY

12.1 Mechanism of Action

Epinephrine acts on both alpha- and beta-adrenergic receptors.

12.2 Pharmacodynamics

Through its action on alpha-adrenergic receptors, epinephrine lessens the vasodilation and increased vascular permeability that occurs during anaphylaxis, which can lead to loss of intravascular fluid volume and hypotension.

Through its action on beta-adrenergic receptors, epinephrine causes bronchial smooth muscle relaxation and helps alleviate bronchospasm, wheezing and dyspnea that may occur during anaphylaxis.

Epinephrine also alleviates pruritus, urticaria, and angioedema and may relieve gastrointestinal and genitourinary symptoms associated with anaphylaxis because of its relaxer effects on the smooth muscle of the stomach, intestine, uterus and urinary bladder.

When given subcutaneously or intramuscularly, epinephrine has a rapid onset and short duration of action.

13 NONCLINICAL TOXICOLOGY

13.1 Carcinogenesis, Mutagenesis, Impairment of Fertility

Long-term studies to evaluate the carcinogenic potential of epinephrine have not been conducted.

Epinephrine and other catecholamines have been shown to have mutagenic potential in vitro and to be an oxidative mutagen in a WP2 bacterial reverse mutation assay.

Epinephrine was positive in the DNA Repair test with B. subtilis (REC) assay, but was not mutagenic in the Salmonella bacterial reverse mutation assay.

The potential for epinephrine to impair fertility has not been evaluated.

This should not prevent the use of epinephrine under the conditions noted under Indications and Usage (1).

16 HOW SUPPLIED/STORAGE AND HANDLING

16.1 How Supplied

Epinephrine Injection, USP Auto-Injectors, 0.3 mg (epinephrine injections, USP 0.3 mg/0.3 mL) are available as NDC 49502-102-02, a pack that contains two Epinephrine Injection, USP Auto-Injectors, 0.3 mg (epinephrine injections, USP 0.3 mg/0.3 mL) and one Epinephrine Injection, USP Auto-Injector Trainer device.

Epinephrine Injection, USP Auto-Injectors, 0.15 mg (epinephrine injections, USP 0.15 mg/0.3 mL) are available as NDC 49502-101-02, a pack that contains two Epinephrine Injection, USP Auto-Injectors, 0.15 mg (epinephrine injections, USP 0.15 mg/0.3 mL) and one Epinephrine Injection, USP Auto-Injector Trainer device.

Epinephrine Injection, USP Auto-Injectors also include an S-clip to clip two carrier tubes together.

Rx only

16.2 Storage and Handling

Protect from light. Epinephrine is light sensitive and should be stored in the carrier tube provided to protect it from light. Store at 20° to 25°C (68° to 77°F); excursions permitted to 15° to 30°C (59° to 86°F) [See USP Controlled Room Temperature]. Do not refrigerate. Before using, check to make sure the solution in the auto-injector is clear and colorless. Replace the auto-injector if the solution is discolored (pinkish or brown color), cloudy, or contains particles.

17 PATIENT COUNSELING INFORMATION

[ See FDA-Approved Patient Labeling (Patient Information and Instructions for Use). ]

A healthcare provider should review the patient instructions and operation of epinephrine injection, USP auto-injector in detail, with the patient or caregiver.

Epinephrine is essential for the treatment of anaphylaxis. Patients who are at risk of or with a history of severe allergic reactions (anaphylaxis) to insect stings or bites, foods, drugs, and other allergens, as well as idiopathic and exercise-induced anaphylaxis, should be carefully instructed about the circumstances under which epinephrine should be used.

Administration and Training

Instruct patients and/or caregivers in the appropriate use of epinephrine injection, USP auto-injector. Epinephrine injection, USP auto-injector should be injected into the middle of the outer thigh (through clothing, if necessary). Each device is a single-use injection. Advise patients to seek immediate medical care in conjunction with administration of epinephrine injection, USP auto-injectors.

Instruct caregivers to hold the leg of young children firmly in place and limit movement prior to and during injection. Lacerations, bent needles, and embedded needles have been reported when epinephrine injection, USP auto-injector has been injected into the thigh of young children who are uncooperative and kick or move during an injection [ see Warnings and Precautions (5.2)].

Complete patient information, including dosage, directions for proper administration and precautions can be found inside each epinephrine injection, USP auto-injector carton. A printed label on the surface of epinephrine injection, USP auto-injector shows instructions for use and a diagram depicting the injection process.

Instruct patients and/or caregivers to use and practice with the Trainer to familiarize themselves with the use of epinephrine injection, USP auto-injector in an allergic emergency. The Trainer may be used multiple times. A Trainer device is provided in epinephrine injection, USP auto-injector cartons.

Adverse Reactions

Epinephrine may produce symptoms and signs that include an increase in heart rate, the sensation of a more forceful heartbeat, palpitations, sweating, nausea and vomiting, difficulty breathing, pallor, dizziness, weakness or shakiness, headache, apprehension, nervousness, or anxiety. These signs and symptoms usually subside rapidly, especially with rest, quiet and recumbency. Patients with hypertension or hyperthyroidism may develop more severe or persistent effects, and patients with coronary artery disease could experience angina. Patients with diabetes may develop increased blood glucose levels following epinephrine administration. Patients with Parkinson’s disease may notice a temporary worsening of symptoms [ see Warnings and Precautions (5.5)] .

Accidental Injection

Advise patients to seek immediate medical care in the case of accidental injection. Since epinephrine is a strong vasoconstrictor when injected into the digits, hands, or feet, treatment should be directed at vasodilatation if there is such an accidental injection to these areas [ see Warnings and Precautions (5.2)].

Serious Infections at the Injection Site

Rare cases of serious skin and soft tissue infections, including necrotizing fasciitis and myonecrosis caused by Clostridia (gas gangrene), have been reported at the injection site following epinephrine injection for anaphylaxis. Advise patients to seek medical care if they develop signs or symptoms of infection, such as persistent redness, warmth, swelling, or tenderness, at the epinephrine injection site [ see Warnings and Precautions (5.3)].

Storage and Handling

Instruct patients to inspect the epinephrine solution visually through the clear window of the auto-injector periodically. Replace epinephrine injection, USP auto-injector if the epinephrine solution appears discolored (pinkish or brown color), cloudy, or contains particles. Epinephrine is light sensitive and should be stored in the carrier tube provided to protect it from light. The carrier tube is not waterproof. Instruct patients that epinephrine injection, USP auto-injector must be used or properly disposed once the blue safety release is removed or after use [ see Storage and Handling (16.2)].

Complete patient information, including dosage, directions for proper administration and precautions can be found inside each epinephrine injection, USP auto-injector carton.

Manufactured for Mylan Specialty L.P., Morgantown, WV 26505, U.S.A. by Meridian Medical Technologies, Inc., Columbia, MD 21046, U.S.A., a Pfizer company

Copyright © 2017 Meridian Medical Technologies. All rights reserved.

Revised: 2/2017
MS:EPIG:R2
0001997

PATIENT INFORMATION and INSTRUCTIONS FOR USE

Epinephrine Injection, USP Auto-Injector 0.3 mg
one dose of 0.3 mg epinephrine, USP 0.3 mg/0.3 mL

Epinephrine Injection, USP Auto-Injector 0.15 mg
one dose of 0.15 mg epinephrine, USP 0.15 mg/0.3 mL

Authorized generic for EpiPen® and EpiPen Jr® Auto-Injectors

For allergic emergencies (anaphylaxis)

Patient Information

Read this Patient Information Leaflet carefully before using the epinephrine injection, USP auto-injector and each time you get a refill. There may be new information. You, your parent, caregiver, or others who may be in a position to administer epinephrine injection, USP auto-injector, should know how to use it before you have an allergic emergency.

This information does not take the place of talking with your healthcare provider about your medical condition or your treatment.

What is the most important information I should know about the Epinephrine Injection, USP Auto-Injector?

1. Epinephrine injection, USP auto-injector contains epinephrine, a medicine used to treat allergic emergencies (anaphylaxis). Anaphylaxis can be life threatening, can happen within minutes, and can be caused by stinging and biting insects, allergy injections, foods, medicines, exercise, or unknown causes.
  Symptoms of anaphylaxis may include:
  1. trouble breathing
  2. wheezing
  3. hoarseness (changes in the way your voice sounds)
  4. hives (raised reddened rash that may itch)
  5. severe itching
  6. swelling of your face, lips, mouth, or tongue
  7. skin rash, redness, or swelling
  8. fast heartbeat
  9. weak pulse
  10. feeling very anxious
  11. confusion
  12. stomach pain
  13. losing control of urine or bowel movements (incontinence)
  14. diarrhea or stomach cramps
  15. dizziness, fainting, or “passing out” (unconsciousness)
2. Always carry your epinephrine injection, USP auto-injector with you because you may not know when anaphylaxis may happen.
  Talk to your healthcare provider if you need additional units to keep at work, school, or other locations. Tell your family members, caregivers, and others where you keep your epinephrine injection, USP auto-injector and how to use it before you need it. You may be unable to speak in an allergic emergency.
3. When you have an allergic emergency (anaphylaxis)
  1. Use epinephrine injection, USP auto-injector right away.
  2. Get emergency medical help right away. You may need further medical attention. You may need to use a second epinephrine injection, USP auto-injector if symptoms continue or recur. Only a healthcare provider should give additional doses of epinephrine if you need more than 2 injections for a single anaphylaxis episode.

What are epinephrine injection, USP auto-injectors?

- Epinephrine injection, USP auto-injectors are disposable, prefilled automatic injection devices (auto-injectors) used to treat life-threatening, allergic emergencies including anaphylaxis in people who are at risk for or have a history of serious allergic emergencies. Each device contains a single dose of epinephrine.
- Epinephrine injection, USP auto-injectors are for immediate self (or caregiver) administration and do not take the place of emergency medical care. You should get emergency help right away after using epinephrine injection, USP auto-injector.
- Epinephrine injection, USP auto-injectors are for people who have been prescribed this medicine by their healthcare provider.
- The epinephrine injection, USP auto-injector (0.3 mg) is for patients who weigh 66 pounds or more (30 kilograms or more).
- The epinephrine injection, USP auto-injector (0.15 mg) is for patients who weigh about 33 to 66 pounds (15 to 30 kilograms).
- It is not known if epinephrine injection, USP auto-injector is safe and effective in children who weigh less than 33 pounds (15 kilograms).

What should I tell my healthcare provider before using the epinephrine injection, USP auto-injector?

Before you use epinephrine injection, USP auto-injector, tell your healthcare provider about all your medical conditions, but especially if you:

- have heart problems or high blood pressure
- have diabetes
- have thyroid problems
- have asthma
- have a history of depression
- have Parkinson’s disease
- have any other medical conditions
- are pregnant or plan to become pregnant. It is not known if epinephrine will harm your unborn baby.
- are breastfeeding or plan to breastfeed. It is not known if epinephrine passes into your breast milk.

Tell your healthcare provider about all the medicines you take, including prescription and over-the-counter medicines, vitamins, and herbal supplements. Tell your healthcare provider of all known allergies.

Especially tell your healthcare provider if you take certain asthma medicines.

Epinephrine injection, USP auto-injector and other medicines may affect each other, causing side effects. Epinephrine injection, USP auto-injector may affect the way other medicines work, and other medicines may affect how epinephrine injection, USP auto-injector works.

Know the medicines you take. Keep a list of them to show your healthcare provider and pharmacist when you get a new medicine.

Use your epinephrine injection, USP auto-injector for treatment of anaphylaxis as prescribed by your healthcare provider, regardless of your medical conditions or the medicines you take.

How should I use epinephrine injection, USP auto-injectors?

- Each epinephrine injection, USP auto-injector contains only 1 dose of medicine.
- Epinephrine injection, USP auto-injector should be injected into the middle of your outer thigh (upper leg). It can be injected through your clothing if needed.
- Read the Instructions for Use at the end of this Patient Information Leaflet about the right way to use epinephrine injection, USP auto-injectors.
- Your healthcare provider will show you how to safely use the epinephrine injection, USP auto-injector.
- Use your epinephrine injection, USP auto-injector exactly as your healthcare provider tells you to use it. You may need to use a second epinephrine injection, USP auto-injector if symptoms continue or recur. Only a healthcare provider should give additional doses of epinephrine if you need more than 2 injections for a single anaphylaxis episode.
- Caution: Never put your thumb, fingers, or hand over the orange tip. Never press or push the orange tip with your thumb, fingers, or hand. The needle comes out of the orange tip. Accidental injection into finger, hands or feet may cause a loss of blood flow to these areas. If this happens, go immediately to the nearest emergency room. Tell the healthcare provider where on your body you received the accidental injection.
- Your epinephrine injection, USP auto-injectors may come packaged with an epinephrine injection, USP auto-injector Trainer and separate Trainer Instructions for Use. The epinephrine injection, USP auto-injector Trainer has a grey color. The grey epinephrine injection, USP auto-injector Trainer contains no medicine and no needle. Periodically practice with your epinephrine injection, USP auto-injector Trainer before an allergic emergency happens to make sure you are able to safely use the real epinephrine injection, USP auto-injector in an emergency. Always carry your real epinephrine injection, USP auto-injector with you in case of an allergic emergency. Additional training resources are available at MyGenericEAI.com.
- Do not drop the carrier tube or auto-injector. If the carrier tube or auto-injector is dropped, check for damage and leakage. Dispose of the auto-injector and carrier tube, and replace if damage or leakage is noticed or suspected.

What are the possible side effects of epinephrine injection, USP auto-injectors?

Epinephrine injection, USP auto-injectors may cause serious side effects.

- The epinephrine injection, USP auto-injector should only be injected into the middle of your outer thigh (upper leg).Do not inject the epinephrine injection, USP auto-injector into your:
  - veins
  - buttocks
  - fingers, toes, hands, or feet
    If you accidentally inject epinephrine injection, USP auto-injector into any other part of your body, go to the nearest emergency room right away. Tell the healthcare provider where on your body you received the accidental injection.
- Rarely, patients who have used epinephrine injection, USP auto-injector may develop infections at the injection site within a few days of an injection. Some of these infections can be serious. Call your healthcare provider right away if you have any of the following at an injection site:
  - redness that does not go away
  - swelling
  - tenderness
  - the area feels warm to the touch
- Cuts on the skin, bent needles, and needles that remain in the skin after the injection, have happened in young children who do not cooperate and kick or move during an injection. If you inject a young child with epinephrine injection, USP auto-injector, hold their leg firmly in place before and during the injection to prevent injuries. Ask your healthcare provider to show you how to properly hold the leg of a young child during injection.
- If you have certain medical conditions, or take certain medicines, your condition may get worse or you may have longer lasting side effects when you use your epinephrine injection, USP auto-injector. Talk to your healthcare provider about all your medical conditions.

Common side effects of epinephrine injection, USP auto-injector include:

- fast, irregular or “pounding” heartbeat
- sweating
- headache
- weakness
- shakiness
- paleness
- feelings of over excitement, nervousness or anxiety
- dizziness
- nausea or vomiting
- breathing problems

These side effects may go away with rest. Tell your healthcare provider if you have any side effect that bothers you or that does not go away.

These are not all the possible side effects of the epinephrine injection, USP auto-injector. For more information, ask your healthcare provider or pharmacist.

Call your healthcare provider for medical advice about side effects. You may report side effects to FDA at 1-800-FDA-1088.

How should I store epinephrine injection, USP auto-injectors?

- Store epinephrine injection, USP auto-injectors at room temperature between 68° to 77°F (20° to 25°C).
- Protect from light.
- Do not expose to extreme cold or heat. For example, do not store in your vehicle’s glove box and do not store in the refrigerator or freezer.
- Examine the contents in the clear window of your auto-injector periodically. The solution should be clear. If the solution is discolored (pinkish or brown color) or contains solid particles, replace the unit.
- Always keep your epinephrine injection, USP auto-injector in the carrier tube to protect it from damage; however, the carrier tube is not waterproof.
- The blue safety release helps to prevent accidental injection. Keep the blue safety release on until you need to use epinephrine injection, USP auto-injector.
- Your epinephrine injection, USP auto-injector has an expiration date. Replace it before the expiration date.

Keep epinephrine injection, USP auto-injectors and all medicines out of the reach of children.

General information about the safe and effective use of epinephrine injection, USP auto-injectors

Medicines are sometimes prescribed for purposes other than those listed in a Patient Information Leaflet. Do not use the epinephrine injection, USP auto-injector for a condition for which it was not prescribed. Do not give your epinephrine injection, USP auto-injector to other people.

This Patient Information Leaflet summarizes the most important information about epinephrine injection, USP auto-injectors. If you would like more information, talk to your healthcare provider. You can ask your pharmacist or healthcare provider for information about epinephrine injection, USP auto-injectors that is written for health professionals.

For more information and video instructions on the use of epinephrine injection, USP auto-injectors, go to MyGenericEAI.com or call 1-800-395-3376.

What are the ingredients in epinephrine injection, USP auto-injectors?

- Active Ingredients: Epinephrine
- Inactive Ingredients: sodium chloride, sodium metabisulfite, hydrochloric acid, and water.

Important Information

- The epinephrine injection, USP auto-injector, 0.3 mg has a yellow colored label.
- The epinephrine injection, USP auto-injector, 0.15 mg has a green colored label.
- The epinephrine injection, USP auto-injector Trainer has a grey color and contains no medicine and no needle.
- Your auto-injector is designed to work through clothing.
- The blue safety release on the epinephrine injection, USP auto-injector helps to prevent accidental injection of the device. Do not remove the blue safety release until you are ready to use it.
- Only inject into the middle of the outer thigh (upper leg). Never inject into any other part of the body.
- Never put your thumb, fingers, or your hand over the orange tip. The needle comes out of the orange tip.
- If an accidental injection happens, get medical help right away.
- Do not place patient information or any other foreign objects in the carrier tube with the auto-injector, as this may prevent you from removing the auto-injector for use.

Instructions for Use

Epinephrine Injection, USP Auto-Injector 0.3 mg
one dose of 0.3 mg epinephrine, USP 0.3 mg/0.3 mL

Epinephrine Injection, USP Auto-Injector 0.15 mg
one dose of 0.15 mg epinephrine, USP 0.15 mg/0.3 mL

For allergic emergencies (anaphylaxis)

Read these Instructions for Use carefully before you use epinephrine injection, USP auto-injector. Before you need to use your epinephrine injection, USP auto-injector, make sure your healthcare provider shows you the right way to use it. Parents, caregivers, and others who may be in a position to administer epinephrine injection, USP auto-injector should also understand how to use it as well. If you have any questions, ask your healthcare provider.

Your epinephrine injection, USP auto-injectors

A dose of epinephrine injection, USP auto-injector requires 3 simple steps: Prepare, Administer and Get emergency medical help

1. Step 1. Prepare epinephrine injection, USP auto-injector for injection

Remove the epinephrine injection, USP auto-injector from the clear carrier tube.

Flip open the yellow cap of your epinephrine injection, USP auto-injector, 0.3 mg or the green cap of your epinephrine injection, USP auto-injector, 0.15 mg carrier tube.

Tip and slide the auto-injector out of the carrier tube.

Grasp the auto-injector in your fist with the orange tip (needle end) pointing downward.

With your other hand, remove the blue safety release by pulling straight up without bending or twisting it.

Note:

- The needle comes out of the orange tip.
- To avoid an accidental injection, never put your thumb, fingers or hand over the orange tip. If an accidental injection happens, get medical help right away.

1. Step 2. Administer epinephrine injection, USP auto-injector

If you are administering epinephrine injection, USP auto-injector to a young child, hold the leg firmly in place while administering an injection.

Place the orange tip against the middle of the outer thigh (upper leg) at a right angle (perpendicular) to the thigh.
Swing and push the auto-injector firmly until it ‘clicks’. The click signals that the injection has started.

Hold firmly in place for 3 seconds (count slowly 1, 2, 3). The injection is now complete.

Remove the auto-injector from the thigh. The orange tip will extend to cover the needle. If the needle is still visible, do not attempt to reuse it.

Massage the injection area for 10 seconds.

1. Step 3. Get emergency medical help now.

You may need further medical attention. You may need to use a second epinephrine injection, USP auto-injector if symptoms continue or recur.

- Take your used auto-injector with you when you go to see a healthcare provider.
- Tell the healthcare provider that you have received an injection of epinephrine. Show the healthcare provider where you received the injection.
- Give your used epinephrine injection, USP auto-injector to the healthcare provider for inspection and proper disposal.
- Ask for a refill, if needed.

Note:

- The used auto-injector with extended needle cover will not fit in the carrier tube.
- Epinephrine injection, USP auto-injectors are single-use injectable devices that deliver a fixed dose of epinephrine. The auto-injector cannot be reused. Do not attempt to reuse epinephrine injection, USP auto-injector after the device has been activated. It is normal for most of the medicine to remain in the auto-injector after the dose is injected. The correct dose has been administered if the orange needle tip is extended and the window is blocked.
- Your epinephrine injection, USP auto-injectors may come packaged with an epinephrine injection, USP auto-injector Trainer and separate Trainer Instructions for Use. The epinephrine injection, USP auto-injector Trainer has a grey color. The grey epinephrine injection, USP auto-injector Trainer contains no medicine and no needle. Practice with your epinephrine injection, USP auto-injector Trainer, but always carry your real epinephrine injection, USP auto-injector in case of an allergic emergency.
- If you will be administering epinephrine injection, USP auto-injector to a young child, ask your healthcare provider to show you how to properly hold the leg in place while administering a dose.
- Do not try to take the epinephrine injection, USP auto-injector apart.

This Patient Information and Instructions for Use has been approved by the U.S. Food and Drug Administration.

Manufactured for:
Mylan Specialty L.P., Morgantown, WV 26505, U.S.A. by Meridian Medical Technologies, Inc., Columbia, MD 21046, U.S.A., a Pfizer company

Copyright © 2017 Meridian Medical Technologies. All rights reserved.

Revised: 2/2017
MS:PIL:EPIG:R2
0001998

Epinephrine Injection, USP Auto-Injector 0.3 mg
one dose of 0.3 mg epinephrine, USP 0.3 mg/0.3 mL

Epinephrine Injection, USP Auto-Injector 0.15 mg
one dose of 0.15 mg epinephrine, USP 0.15 mg/0.3 mL

MyGenericEAI.com

Register your epinephrine injection, USP auto-injector at MyGenericEAI.com and find out more about:

- Free epinephrine injection, USP auto-injector Refill Reminder Program. It is important to keep your auto-injector up-to-date.

Register up to 6 epinephrine injection, USP auto-injectors and receive automatic Refill Reminder Alerts.

- Receive periodic information related to allergies and allergens.
- Instructional Video

For more information about epinephrine injection, USP auto-injectors and proper use of the product, call Mylan at 1-877-446-3679 or visit MyGenericEAI.com.

Epinephrine Injection, USP Auto-Injector Trainer
Instructions for Use

Epinephrine Injection, USP Auto-Injector Trainer Instructions for Use

In an emergency: Do not use the grey Trainer. Use your real yellow epinephrine injection, USP auto-injector, 0.3 mg or green epinephrine injection, USP auto-injector, 0.15 mg.

Important Information

- The Trainer label has a grey color.
- The Trainer contains no medicine and no needle.
- Periodically practice with the grey colored Trainer before an allergic emergency (anaphylaxis) happens to make sure you are able to safely use the real yellow epinephrine injection, USP auto-injector, 0.3 mg or green epinephrine injection, USP auto-injector, 0.15 mg in case of an emergency.
- Always carry your real yellow epinephrine injection, USP auto-injector, 0.3 mg or green epinephrine injection, USP auto-injector, 0.15 mg in case of an allergic emergency.

The Epinephrine Injection, USP Auto-Injector Trainer

Familiarize yourself with this grey Trainer. Practice until you are comfortable using it.

Your grey colored Trainer:

- Never put your thumb, other fingers, or hand over the Orange Tip.
- The Orange Tip is where the needle comes out of your epinephrine injection, USP auto-injector.

Practice Instructions

1 Prepare the Trainer for Simulated Injection

- Grasp the grey Trainer in your fist with the orange tip pointing downward.
- With your other hand, remove blue safety release by pulling straight up without bending or twisting it.
- Removing the blue safety release unlocks the Trainer.

2 Administer the Trainer Simulation

- If practicing with a young child, hold the leg firmly in place while using the epinephrine injection, USP auto-injector Trainer. Ask your healthcare provider to show you how to properly hold the leg to practice so that you will be prepared before an allergic emergency happens.

- Place the orange tip against the middle of the outer thigh (upper leg) at a right angle (perpendicular) to the thigh.
- Swing and push the trainer firmly until it ‘clicks.’ The click signals that the injection has started.

- Hold firmly in place for 3 seconds (count slowly 1,2,3).
- Remove the Trainer from the thigh and massage the injection area for 10 seconds. The orange tip automatically extends out after use.

Note:

- In an actual emergency, you would need to seek medical help right away
- The actual auto-injector is made to work through clothing
- Do not inject into any other part of the body

3 To reset the Trainer

- Put the blue safety release back on the Trainer
- Place the orange tip on a hard surface
- Squeeze the sides of the orange tip and push down on the Trainer with the other hand

Note: With the real yellow epinephrine injection, USP auto-injector, 0.3 mg or green epinephrine injection, USP auto-injector, 0.15 mg, the orange tip covers the needle after self-injection to help protect you from accidentally sticking yourself or others.

Practice Session Information

In case of an allergic emergency, use the real yellow epinephrine injection, USP auto-injector, 0.3 mg or green epinephrine injection, USP auto-injector, 0.15 mg and not the grey Trainer.

Follow instructions above. Repeat as often as needed until you are able to self-inject quickly and correctly.

Reread:

- These Trainer Instructions for Use
- The “Patient Information” that comes with your epinephrine injection, USP auto-injector

Train others who could help you in an emergency:

- Your parents, caregivers, and others who may be in a position to administer epinephrine injection, USP auto-injector should know how to help you during an allergic emergency (anaphylaxis). Before an emergency occurs, have them:
  - Practice activating the Trainer
  - Read these Trainer Instructions and the “Patient Information”

For more information about Epinephrine Injection, USP Auto-Injectors and the proper use of the products, go to MyGenericEAI.com.

Caution:

Important differences between the Trainer and your real yellow epinephrine injection, USP auto-injector, 0.3 mg or green epinephrine injection, USP auto-injector, 0.15 mg

 | TRAINER (Grey) | Epinephrine Injection, USP Auto-Injector, 0.3 mg (Yellow) | Epinephrine Injection, USP Auto-Injector , 0.15 mg (Green)
Contains medication? | NO | YES | YES
Has needle? | NO | YES | YES
Comes in Carrier Tube? | NO | YES | YES
Color of Label? | Grey | Yellow | Green
Has expiration date? | NO | YES | YES
Can be reused? | YES | NO (use only once) | NO (use only once)
Okay to remove and replace safety release? | YES | NO (remove just once before use) | NO (remove just once before use)
Pressure needed to hold against thigh? | Moderate | Strong | Strong

This Trainer Instructions for Use has been approved by the U.S. Food and Drug Administration.

Manufactured for Mylan Specialty L.P., Morgantown, WV 26505, U.S.A. by Meridian Medical Technologies, Inc., Columbia, MD 21046, U.S.A., a Pfizer company

Copyright © 2017 Meridian Medical Technologies. All rights reserved.

Revised: 2/2017
MS:EPITG:R2
0001999

PRINCIPAL DISPLAY PANEL – OUTER PACKAGE LABEL

NDC 71872-7135-1
Rx only

For Allergic Emergencies (Anaphylaxis)

Epinephrine Injection, USP
1 - Auto-Injector 0.3 mg

Authorized generic for
EpiPen® Auto-Injector

For more information about your Epinephrine Injection, USP
Auto-Injectors visit MyGenericEAI.com

Never put your thumb, fingers or hand
over the orange tip.

Never put thumb, fingers or hand over orange tip.
Do not remove blue safety release until ready to use.

Each Epinephrine Injection, USP Auto-Injector delivers one 0.3 mg
intramuscular dose of epinephrine from epinephrine injection, USP
0.3 mg/0.3 mL.

Discard unit after use. The Trainer contains no medicine and no needle.

Replace if discolored. Store at 68° to 77°F
(20° to 25°C). Do not refrigerate.
Protect from light.